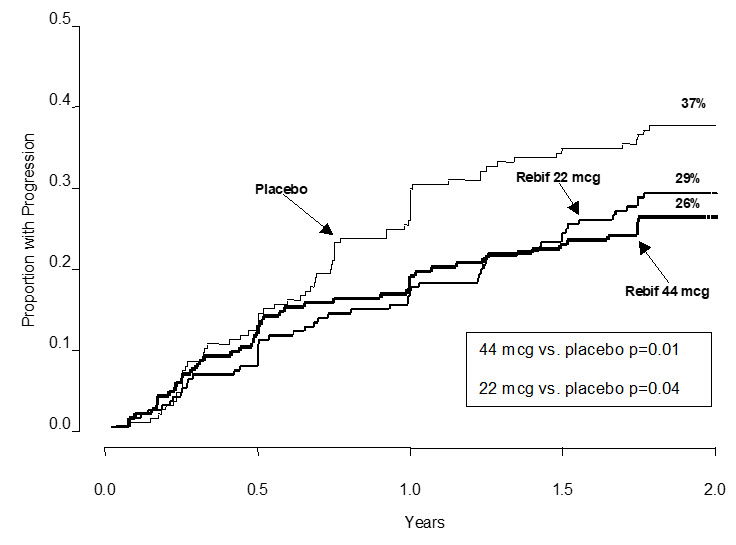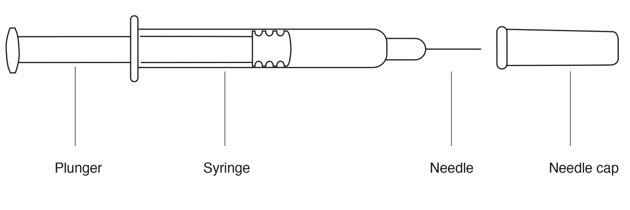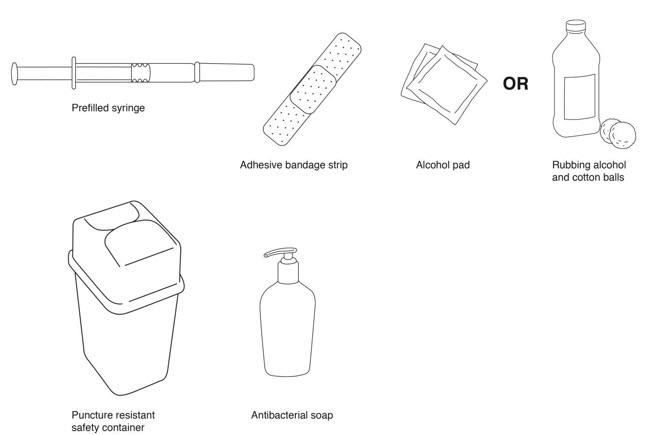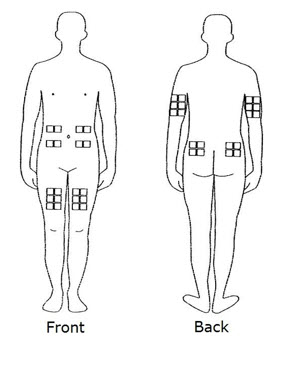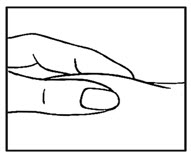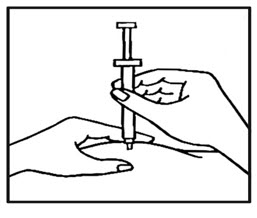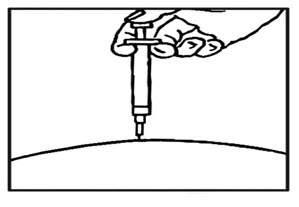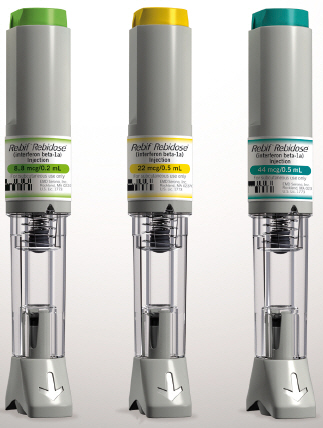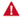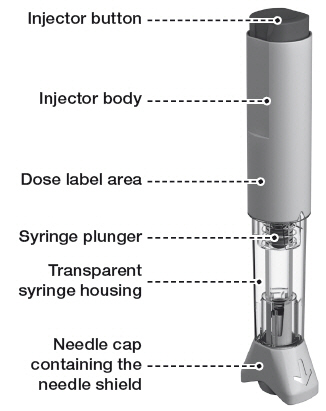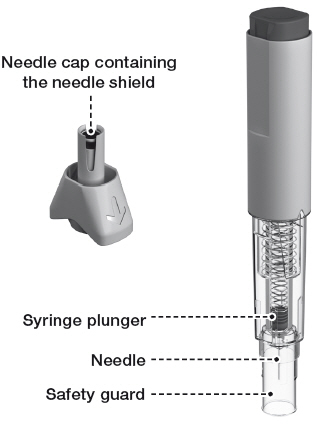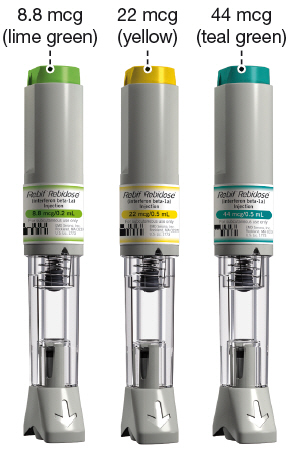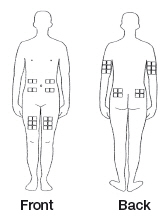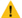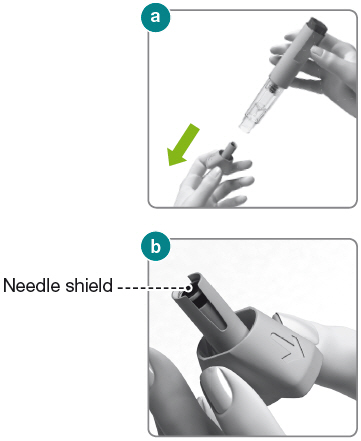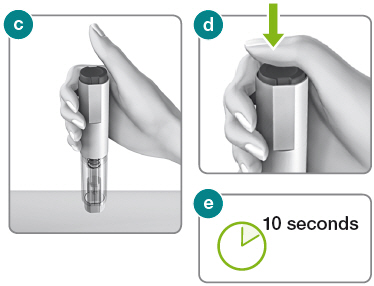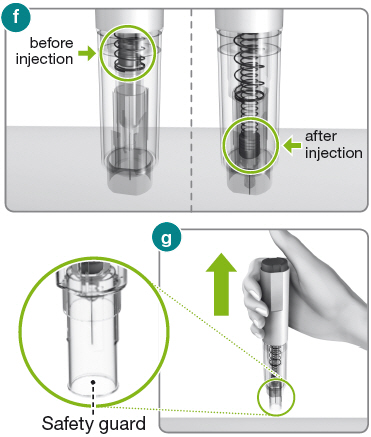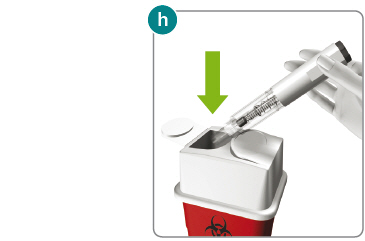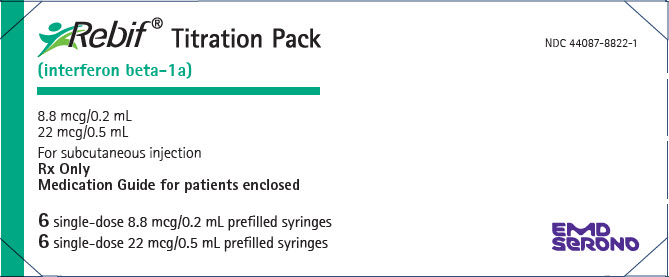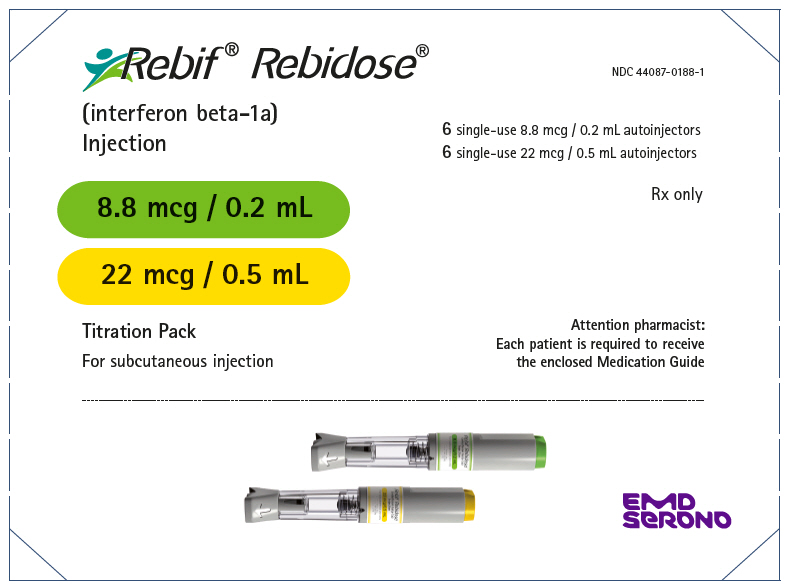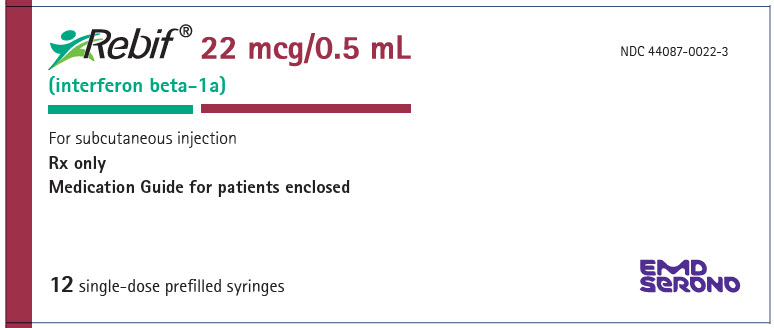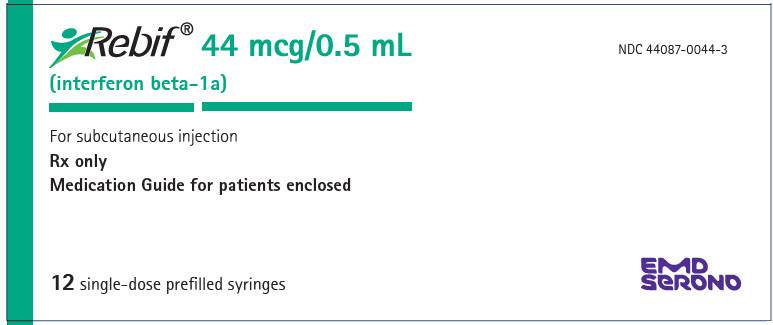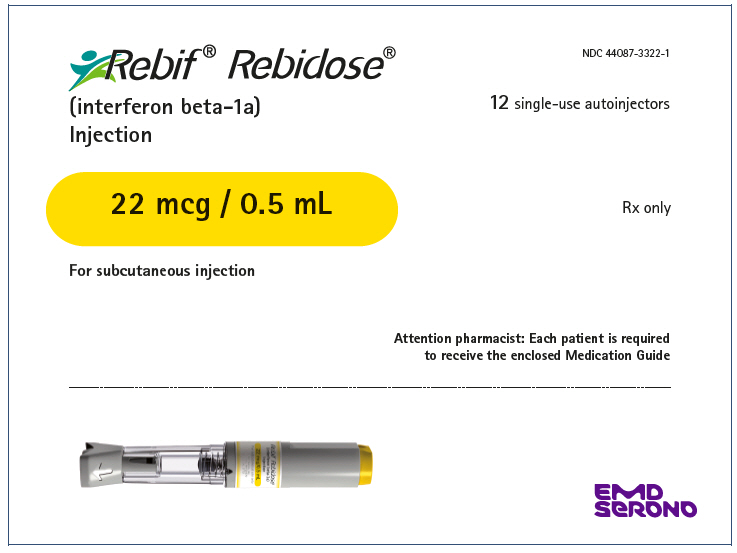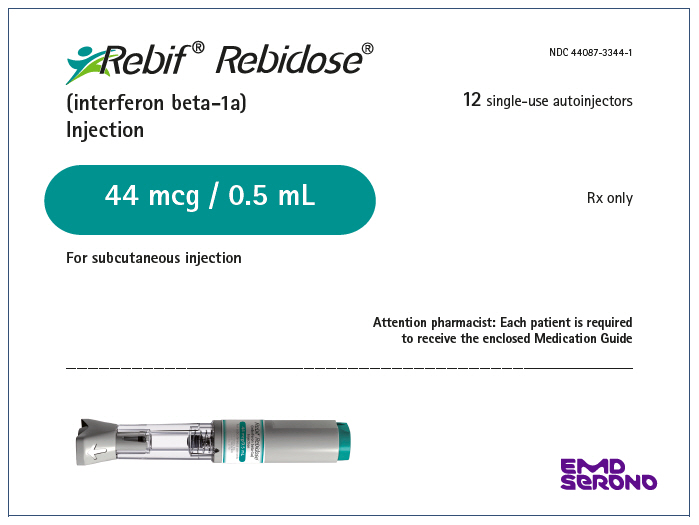 DRUG LABEL: Rebif
NDC: 44087-8822 | Form: KIT | Route: SUBCUTANEOUS
Manufacturer: EMD Serono, Inc.
Category: prescription | Type: HUMAN PRESCRIPTION DRUG LABEL
Date: 20250922

ACTIVE INGREDIENTS: INTERFERON BETA-1A 8.8 ug/0.2 mL; INTERFERON BETA-1A 22 ug/0.5 mL
INACTIVE INGREDIENTS: MANNITOL 10.9 mg/0.2 mL; ALBUMIN HUMAN 0.8 mg/0.2 mL; SODIUM ACETATE 0.16 mg/0.2 mL; WATER; MANNITOL 27.3 mg/0.5 mL; ALBUMIN HUMAN 2 mg/0.5 mL; SODIUM ACETATE 0.4 mg/0.5 mL; WATER

HIGHLIGHTS OF PRESCRIBING INFORMATION

These highlights do not include all the information needed to use REBIF safely and effectively. See full prescribing information for REBIF.
REBIF (interferon beta-1a), for subcutaneous injection
Initial U.S. Approval: 1996

RECENT MAJOR CHANGES

Warnings and Precautions (5.7) | 7/2023

1 INDICATIONS AND USAGE

Rebif is an interferon beta indicated for the treatment of relapsing forms of multiple sclerosis (MS), to include clinically isolated syndrome, relapsing-remitting disease, and active secondary progressive disease, in adults. (1)

2 DOSAGE AND ADMINISTRATION

- For subcutaneous injection only (2.1)
- The recommended dose is either 22 mcg or 44 mcg injected subcutaneously three times per week (2.1)
- Titration: Generally, the starting dose should be 20% of the prescribed dose three times per week, and increased over a 4 week period to the targeted recommended dose of either 22 mcg or 44 mcg injected subcutaneously three times per week (2.1)
- Analgesics and/or antipyretics on treatment days may help ameliorate flu-like symptoms (2.3)

3 DOSAGE FORMS AND STRENGTHS

- Injection: 8.8 mcg in 0.2 mL, and 22 mcg or 44 mcg in 0.5 mL in single-dose prefilled syringe (3)
- Injection: 8.8 mcg in 0.2 mL, and 22 mcg or 44 mcg in 0.5 mL in single-dose autoinjector (3)

4 CONTRAINDICATIONS

- History of hypersensitivity to natural or recombinant interferon beta, human albumin, or any other component of the formulation (4)

5 WARNINGS AND PRECAUTIONS

- Depression and Suicide: Advise patients to immediately report any symptoms of depression and/or suicidal ideation; consider discontinuation of REBIF if depression occurs (5.1)
- Hepatic Injury: Monitor liver function tests; monitor patients for signs and symptoms of hepatic injury; consider discontinuing REBIF if hepatic injury occurs (5.2)
- Anaphylaxis and Other Allergic Reactions: Discontinue REBIF if anaphylaxis occurs (5.3)
- Injection Site Reactions Including Necrosis: Do not administer REBIF into affected area until fully healed; if multiple lesions occur, change injections sites or discontinue REBIF until healing of skin lesions (5.4)
- Decreased Peripheral Blood Counts: Monitor complete blood counts (5.5)
- Thrombotic Microangiopathy: Cases of thrombotic microangiopathy have been reported. Discontinue REBIF if clinical symptoms and laboratory findings consistent with TMA occur (5.6).
- Pulmonary Arterial Hypertension: Cases of pulmonary arterial hypertension (PAH) have been reported in patients treated with interferon beta products, including REBIF. Discontinue REBIF if PAH is diagnosed (5.7)
- Seizures: Monitor for seizures when administering REBIF to patients, particularly those with pre-existing seizure disorders (5.8)

6 ADVERSE REACTIONS

- The most common adverse reactions in controlled clinical trials were injection site disorders, influenza-like symptoms, abdominal pain, depression, elevation of liver enzymes and hematologic abnormalities (6.1)

To report SUSPECTED ADVERSE REACTIONS, contact EMD Serono at 1-800-283-8088 ext. 5563 or FDA at 1-800-FDA-1088 or www.fda.gov/medwatch

8 USE IN SPECIFIC POPULATIONS

- Pregnancy: Epidemiological data do not suggest a clear relationship between interferon beta use and major congenital malformations, but interferon beta may cause fetal harm based on animal data (8.1).

FULL PRESCRIBING INFORMATION

1 INDICATIONS AND USAGE

REBIF is indicated for the treatment of relapsing forms of multiple sclerosis (MS), to include clinically isolated syndrome, relapsing-remitting disease, and active secondary progressive disease, in adults.

2 DOSAGE AND ADMINISTRATION

2.1 Dosing Information

The recommended dose of REBIF is either 22 mcg or 44 mcg injected subcutaneously three times per week. REBIF should be administered, if possible, at the same time (preferably in the late afternoon or evening) on the same three days (e.g., Monday, Wednesday, and Friday) at least 48 hours apart each week.

Generally, patients should be started at 20% of the prescribed dose three times per week and increased over a 4-week period to the targeted dose, either 22 mcg three times per week (see Table 1) or 44 mcg three times per week (see Table 2). Patients prescribed a targeted dose of 22 mcg three times per week should use the prefilled syringes for titration.

A Titration Pack containing 6 doses of 8.8 mcg (0.2 mL) and 6 doses of 22 mcg (0.5 mL) is available for use during the titration period in both REBIF prefilled syringes and REBIF Rebidose autoinjectors.

Table 1: Titration Schedule for a 22 mcg Prescribed Dose [Use only prefilled syringes, not autoinjectors, to titrate to the 22 mcg Prescribed Dose]
Week of Use | Dose | Syringe to Use | Amount of syringe
Week 1 Titration | 4.4 mcg | 8.8 mcg syringe | Use half of syringe
Week 2 Titration | 4.4 mcg | 8.8 mcg syringe | Use half of syringe
Week 3 Titration | 11 mcg | 22 mcg syringe | Use half of syringe
Week 4 Titration | 11 mcg | 22 mcg syringe | Use half of syringe
Week 5 and after | 22 mcg | 22 mcg syringe or autoinjector | Use full syringe or autoinjector

Table 2: Titration Schedule for a 44 mcg Prescribed Dose [Prefilled syringes or autoinjectors can be used to titrate to the 44 mcg Prescribed Dose]
Week of Use | Dose | Syringe or Autoinjector to Use | Amount of syringe or autoinjector
Week 1 Titration | 8.8 mcg | 8.8 mcg syringe or autoinjector | Use full syringe or autoinjector
Week 2 Titration | 8.8 mcg | 8.8 mcg syringe or autoinjector | Use full syringe or autoinjector
Week 3 Titration | 22 mcg | 22 mcg syringe or autoinjector | Use full syringe or autoinjector
Week 4 Titration | 22 mcg | 22 mcg syringe or autoinjector | Use full syringe or autoinjector
Week 5 and after | 44 mcg | 44 mcg syringe or autoinjector | Use full syringe or autoinjector

Decreased peripheral blood counts or elevated liver function tests may necessitate dose reduction or discontinuation of REBIF administration until toxicity is resolved [see Warnings and Precautions (5.2, 5.5) and Adverse Reactions (6)].

2.2 Important Administration Instructions

REBIF is intended for use under the guidance and supervision of a physician. It is recommended that physicians or qualified medical personnel train patients in the proper technique for self-administering subcutaneous injections using the prefilled syringe or injection device approved for use with REBIF. Injection depth of the REBIF Rebidose autoinjector is fixed at 8 mm; the healthcare provider should determine the injection technique.

The initial injection should be performed under the supervision of an appropriately qualified healthcare provider.

Appropriate instruction for self-injection or injection by another person should be provided to the patient or their caregiver, including careful review of the REBIF Medication Guide and the REBIF Rebidose autoinjector Instructions for Use that accompanies the product. Users should demonstrate competency in all aspects of the injection prior to independent use. If a patient is to self-administer REBIF, the physical and cognitive ability of that patient to self-administer and properly dispose of prefilled syringes or the REBIF Rebidose autoinjectors should be assessed. Patients with severe neurological deficits should not self-administer injections without assistance from a trained caregiver.

Advise patients and caregivers to:

- visually inspect REBIF for particulate matter and discoloration prior to administration
- use aseptic technique when administering REBIF
- rotate site of injection with each dose to minimize the likelihood of severe injection site reactions, including necrosis or localized infection [see Warnings and Precautions (5.4)]
- use a puncture-resistant container for safe disposal of used needles, prefilled syringes and REBIF Rebidose autoinjectors
- do not re-use needles, syringes or REBIF Rebidose autoinjectors

2.3 Premedication for Flu-like Symptoms

Concurrent use of analgesics and/or antipyretics may help ameliorate flu-like symptoms associated with REBIF use on treatment days.

3 DOSAGE FORMS AND STRENGTHS

- Injection: 8.8 mcg per 0.2 mL in a graduated, single-dose REBIF prefilled syringe
- Injection: 22 mcg per 0.5 mL in a graduated, single-dose REBIF prefilled syringe
- Injection: 44 mcg per 0.5 mL in a graduated, single-dose REBIF prefilled syringe
- Injection: 8.8 mcg per 0.2 mL in a single-dose prefilled REBIF Rebidose autoinjector
- Injection: 22 mcg per 0.5 mL in a single-dose prefilled REBIF Rebidose autoinjector
- Injection: 44 mcg per 0.5 mL in a single-dose prefilled REBIF Rebidose autoinjector

4 CONTRAINDICATIONS

REBIF is contraindicated in patients with a history of hypersensitivity to natural or recombinant interferon beta, human albumin, or any other component of the formulation.

5 WARNINGS AND PRECAUTIONS

5.1 Depression and Suicide

REBIF (interferon beta-1a) should be used with caution in patients with depression, a condition that is common in people with multiple sclerosis. Depression, suicidal ideation, and suicide attempts have been reported to occur with increased frequency in patients receiving interferon compounds, including REBIF. In addition, there have been postmarketing reports of suicide in patients treated with REBIF. Patients should be advised to report immediately any symptoms of depression and/or suicidal ideation to the prescribing physician. If a patient develops depression, cessation of treatment with REBIF should be considered.

5.2 Hepatic Injury

Severe liver injury, including some cases of hepatic failure requiring liver transplantation, has been reported rarely in patients taking REBIF. Symptoms of liver dysfunction began from one to six months following the initiation of REBIF. If jaundice or other symptoms of liver dysfunction appear, treatment with REBIF should be discontinued immediately due to the potential for rapid progression to liver failure.

Asymptomatic elevation of hepatic transaminases (particularly SGPT) is common with interferon therapy [see Adverse Reactions (6.1)]. REBIF should be initiated with caution in patients with active liver disease, alcohol abuse, increased serum SGPT (> 2.5 times ULN), or a history of significant liver disease. Also, the potential risk of REBIF used in combination with known hepatotoxic products should be considered prior to REBIF administration, or when adding new agents to the regimen of patients already on REBIF. Reduction of REBIF dose should be considered if SGPT rises above 5 times the upper limit of normal. The dose may be gradually re-escalated when enzyme levels have normalized [see Warnings and Precautions (5.9) and Dosage and Administration (2.1)].

5.3 Anaphylaxis and Other Allergic Reactions

Anaphylaxis has been reported as a rare complication of REBIF use. Other allergic reactions have included skin rash and urticaria, and have ranged from mild to severe without a clear relationship to dose or duration of exposure. Several allergic reactions, some severe, have occurred after prolonged use. Discontinue REBIF if anaphylaxis occurs.

5.4 Injection Site Reactions Including Necrosis

Injection site reactions, including injection site necrosis, can occur with the use of interferon beta products, including REBIF. In controlled clinical trials, injection site reactions occurred more frequently in REBIF-treated patients (92% in the 44 mcg group and 89% in the 22 mcg group) than in placebo-treated patients (39%) and at a higher frequency in REBIF treated patients (83%) than in AVONEX-treated patients (28%). Injection site necrosis also occurred more frequently in REBIF-treated patients (3% in the 44 mcg group and 1% in the 22 mcg group) than in placebo- treated patients (0) during the two years of therapy.

Injection site reactions including injection site pain, erythema, edema, cellulitis, abscess, and necrosis have been reported in the postmarketing setting. Some occurred more than 2 years after initiation of REBIF. Necrosis occurred at single and at multiple injection sites. Some cases of injection site necrosis required treatment with intravenous antibiotics and surgical intervention (debridement and skin grafting). Some cases of injection site abscesses and cellulitis required treatment with hospitalization for surgical drainage and intravenous antibiotics.

Patient understanding and use of aseptic self-injection techniques and procedures should be periodically evaluated, particularly if injection site necrosis has occurred. Patients should be advised of the importance of rotating sites of injection with each dose and not reusing syringes. Patients should be advised against injecting an area which is inflamed, edematous, erythematous, ecchymotic, or has any other signs of infection. These signs should be reported to a healthcare professional immediately. If multiple lesions occur, change injection site or discontinue therapy until healing occurs.

5.5 Decreased Peripheral Blood Counts

Decreased peripheral blood counts in all cell lines, including pancytopenia, have been reported in REBIF-treated patients. In controlled clinical trials, leukopenia occurred at a higher frequency in REBIF-treated patients (36% in 44 mcg group and 28% in 22 mcg group) than in placebo-treated patients (14%) and at a higher frequency in REBIF-treated patients (6%) compared to the AVONEX-treated patients (<1%). Thrombocytopenia and anemia occurred more frequently in 44 mcg REBIF-treated patients (8% and 5%, respectively) than in placebo-treated patients (2% and 3%, respectively). In a pooled analysis of 7 placebo controlled trials with REBIF doses of 22 mcg or 44 mcg, the rate of pancytopenia (in subjects with normal baseline values who developed laboratory values less than the lower limit of normal for all 3 hematology parameters simultaneously) was higher in the total REBIF group (5.5 per 1000 subject-year) than in the placebo group (1.2 per 1000 subject-year). Patients should be monitored for symptoms or signs of decreased blood counts. Monitoring of complete blood and differential white blood cell counts is also recommended [see Dosage and Administration (2.1) and Warnings and Precautions (5.9)].

5.6 Thrombotic Microangiopathy

Cases of thrombotic microangiopathy (TMA), including thrombotic thrombocytopenic purpura and hemolytic uremic syndrome, some fatal, have been reported with interferon beta products, including REBIF. Cases have been reported several weeks to years after starting interferon beta products. Discontinue REBIF if clinical symptoms and laboratory findings consistent with TMA occur, and manage as clinically indicated.

5.7 Pulmonary Arterial Hypertension

Cases of pulmonary arterial hypertension (PAH) have been reported with interferon beta products, including REBIF. PAH has occurred in patients treated with interferon beta products in the absence of other contributory factors. Many of the reported cases required hospitalization, including one case with interferon beta in which the patient underwent a lung transplant. PAH has developed at various time points after initiating therapy with interferon beta products and may occur several years after starting treatment.

Patients who develop unexplained symptoms (e.g., dyspnea, new or increasing fatigue) should be assessed for PAH. If alternative etiologies have been ruled out and a diagnosis of PAH is confirmed, discontinue treatment and manage as clinically indicated.

5.8 Seizures

Caution should be exercised when administering REBIF to patients with pre-existing seizure disorders. Seizures have been temporally associated with the use of beta interferons, including REBIF, in clinical trials and in postmarketing reports.

5.9 Laboratory Tests

In addition to those laboratory tests normally required for monitoring patients with multiple sclerosis, blood cell counts and liver function tests are recommended at regular intervals (1, 3, and 6 months) following introduction of REBIF therapy and then periodically thereafter in the absence of clinical symptoms. Patients with myelosuppression may require more intensive monitoring of complete blood cell counts, with differential and platelet counts [see Dosage and Administration (2.1) and Warnings and Precautions (5.5)]. New or worsening thyroid abnormalities have developed in some patients treated with REBIF. Thyroid function tests are recommended every 6 months in patients with a history of thyroid dysfunction or as clinically indicated.

6 ADVERSE REACTIONS

The following adverse reactions are discussed in more detail in the Warnings and Precautions section of the label:

- Depression and Suicide [see Warnings and Precautions (5.1)]
- Hepatic Injury [see Warnings and Precautions (5.2)]
- Anaphylaxis and Other Allergic Reactions [see Warnings and Precautions (5.3)]
- Injection Site Reactions including Necrosis [see Warnings and Precautions (5.4)]
- Decreased Peripheral Blood Counts [see Warnings and Precautions (5.5)]
- Thrombotic Microangiopathy [see Warnings and Precautions (5.6)]
- Pulmonary Arterial Hypertension [ see Warnings and Precautions (5.7)]
- Seizures [see Warnings and Precautions (5.8)]
- Laboratory Tests [see Warnings and Precautions (5.9)]

6.1 Clinical Trial Experience

Because clinical trials are conducted under widely varying conditions, adverse reaction rates observed in the clinical trials of REBIF cannot be directly compared to rates in the clinical trials of other drugs and may not reflect the rates observed in practice.

A total of 712 patients with relapsing-remitting multiple sclerosis (RRMS) in two controlled clinical trials took REBIF (22 mcg or 44 mcg given three times per week) [see Clinical Studies (14)]. Ages ranged from 18 to 55 years. Nearly three-fourths of the patients were female, and more than 90% were Caucasian, largely reflecting the general demographics of the population of patients with multiple sclerosis.

The most commonly reported adverse reactions were injection site disorders, influenza-like symptoms (headache, fatigue, fever, rigors, chest pain, back pain, myalgia), abdominal pain, depression, elevation of liver enzymes and hematologic abnormalities. The most frequently reported adverse reactions resulting in clinical intervention (e.g., discontinuation of REBIF, adjustment in dosage, or the need for concomitant medication to treat an adverse reaction were injection site disorders, influenza-like symptoms, depression, and elevation of liver enzymes [see Warnings and Precautions (5)].

Study 1 was a 2-year placebo-controlled study in RRMS patients treated with REBIF 22 mcg (n=189), 44 mcg (n=184), or placebo (n=187). Table 3 enumerates adverse reactions and laboratory abnormalities that occurred at an incidence that was at least 2% more in either REBIF-treated group than was observed in the placebo group.

Table 3. Adverse Reactions and Laboratory Abnormalities in Study 1
Body System | Placebo tiw (n=187) | REBIF 22 mcg tiw (n=189) | REBIF 44 mcg tiw (n=184)
Preferred Term | % | % | %
BODY AS A WHOLE
Influenza-like symptoms | 51 | 56 | 59
Headache | 63 | 65 | 70
Fatigue | 36 | 33 | 41
Fever | 16 | 25 | 28
Rigors | 5 | 6 | 13
Chest pain | 5 | 6 | 8
Malaise | 1 | 4 | 5
INJECTION SITE DISORDERS
Injection Site Reaction | 39 | 89 | 92
Injection Site Necrosis | 0 | 1 | 3
NERVOUS SYSTEM DISORDERS
Hypertonia | 5 | 7 | 6
Coordination Abnormal | 2 | 5 | 4
Convulsions | 2 | 5 | 4
Somnolence | 1 | 4 | 5
ENDOCRINE DISORDERS
Thyroid Disorder | 3 | 4 | 6
GASTROINTESTINAL SYSTEM DISORDERS
Abdominal Pain | 17 | 22 | 20
Dry Mouth | 1 | 1 | 5
LIVER AND BILIARY SYSTEM DISORDERS
SGPT Increased | 4 | 20 | 27
SGOT Increased | 4 | 10 | 17
Bilirubinemia | 1 | 3 | 2
MUSCULO-SKELETAL SYSTEM DISORDERS
Myalgia | 20 | 25 | 25
Back Pain | 20 | 23 | 25
Skeletal Pain | 10 | 15 | 10
HEMATOLOGIC DISORDERS
Leukopenia | 14 | 28 | 36
Lymphadenopathy | 8 | 11 | 12
Thrombocytopenia | 2 | 2 | 8
Anemia | 3 | 3 | 5
SKIN DISORDERS
Rash Erythematous | 3 | 7 | 5
Rash Maculo-Papular | 2 | 5 | 4
Hyperhidrosis | 2 | 4 | 4
URINARY SYSTEM DISORDERS
Micturition Frequency | 4 | 2 | 7
Urinary Incontinence | 2 | 4 | 2
VISION DISORDERS
Vision Abnormal | 7 | 7 | 13
Xerophthalmia | 0 | 3 | 1

Adverse reactions in Study 2, a 1-year active-controlled (vs. interferon beta-1a, 30 mcg once weekly intramuscular injection, n=338) study including 339 patients with MS treated with REBIF were generally similar to those in Study 1, taking into account the disparity in study durations.

6.2 Immunogenicity

Anaphylaxis and other allergic reactions have been observed with the use of REBIF [see Warnings and Precautions (5.3)]. As with all therapeutic proteins, there is a potential for immunogenicity. In Study 1, the presence of neutralizing antibodies (NAb) to REBIF was determined by collecting and analyzing serum pre-study and at 6 month time intervals during the 2 years of the clinical trial. Serum NAb were detected in 59/189 (31%) and 45/184 (24%) of REBIF-treated patients at the 22 mcg and 44 mcg three times per week doses, respectively, at one or more times during the study. The data reflect the percentage of patients whose test results were considered positive for antibodies to REBIF using an antiviral cytopathic effect assay, and are highly dependent on the sensitivity and specificity of the assay. Additionally, the observed incidence of NAb positivity in an assay may be influenced by several factors including sample handling, timing of sample collection, concomitant medications and underlying disease. For these reasons, comparison of the incidence of antibodies to REBIF with the incidence of antibodies to other products may be misleading.

6.3 Postmarketing Experience

The following adverse reactions have been identified during post-approval use of REBIF. Because these reactions are reported voluntarily from a population of uncertain size, it is not always possible to reliably estimate their frequency or establish a causal relationship to drug exposure.

Autoimmune Disorders: Drug-induced lupus erythematosus, autoimmune hepatitis

Eye Disorders: Retinal vascular disorders (i.e. retinopathy, cotton wool spots or obstruction of retinal artery or vein)

Respiratory, Thoracic and mediastinal disorders: Pulmonary Arterial Hypertension

Skin and Subcutaneous Tissue Disorders: Erythema multiforme, Stevens-Johnson syndrome

Blood and Lymphatic System Disorders: Hemolytic anemia

8 USE IN SPECIFIC POPULATIONS

8.1 Pregnancy

Risk Summary

Data from a large population-based cohort study, as well as other published studies over several decades, have not identified a drug-associated risk of major birth defects with the use of interferon beta during early pregnancy. Findings regarding a potential risk for low birth weight or miscarriage with the use of interferon beta in pregnancy have been inconsistent (see Data). It is unclear whether, as a class of products, administration of interferon beta therapies to pregnant animals at doses greater than those used clinically results in an increased rate of abortion. The potential for REBIF to have adverse effects on embryofetal development has not been fully assessed in animals [see Data].

In the U.S. general population, the estimated background risk of major birth defects and miscarriage in clinically recognized pregnancies is 2% to 4% and 15% to 20%, respectively. The background risk of major birth defects and miscarriage for the indicated population is unknown.

Data

Human data

The majority of observational studies reporting on pregnancies exposed to interferon beta products did not identify an association between the use of interferon beta products during early pregnancy and an increased risk of major birth defects.

In a population-based cohort study conducted in Finland and Sweden, data were collected from 1996—2014 in Finland and from 2005—2014 in Sweden on 2,831 pregnancy outcomes from women with MS. 797 pregnancies were in women exposed to interferon beta only. No evidence was found of an increased risk of major birth defects among women with MS exposed to interferon beta products compared to women with MS that were unexposed to any non-steroid therapy for MS (n=1,647) within the study. No increased risks were observed for miscarriages and ectopic pregnancies, though there were limitations in obtaining complete data capture for these outcomes, making the interpretation of the findings more difficult.

Two small cohort studies that examined pregnancies exposed to interferon beta products (without differentiating between subtypes of interferon beta products) suggested that a decrease in mean birth weight may be associated with interferon beta exposure during pregnancy, but this finding was not confirmed in larger observational studies. Two small studies observed an increased prevalence of miscarriage, although the finding was only statistically significant in one study. Most studies enrolled patients later in pregnancy, which made it difficult to ascertain the true percentage of miscarriages. In one small cohort study, a significantly increased risk of preterm birth following interferon beta exposure during pregnancy was observed.

Animal data

In a study in pregnant cynomolgus monkeys, interferon beta was administered daily (intramuscular doses approximately 1, 2, and 7 times the maximum recommended cumulative weekly human dose, based on body surface area) either throughout the period of organogenesis or later in pregnancy (gestation day 90 to term). No adverse effects on embryofetal development were observed; however, the possibility of adverse effects cannot be ruled out because of the small number of animals tested (six per dose group at each developmental period).

8.2 Lactation

Risk Summary

Limited published literature has described the presence of interferon beta-1a products in human milk at low levels. There are no data on the effects of interferon beta-1a on milk production. Therefore, the developmental and health benefits of breastfeeding should be considered along with the mother's clinical need for REBIF and any potential adverse effects on the breastfed child from REBIF or from the underlying maternal condition.

8.4 Pediatric Use

Safety and effectiveness in pediatric patients have not been established.

8.5 Geriatric Use

Clinical studies of REBIF did not include sufficient numbers of subjects aged 65 and over to determine whether they respond differently than younger subjects. In general, dose selection for an elderly patient should be cautious, usually starting at the low end of the dosing range, reflecting the greater frequency of decreased hepatic, renal or cardiac function, and of concomitant disease or other drug therapy.

11 DESCRIPTION

REBIF (interferon beta-1a) is a purified 166 amino acid glycoprotein with a molecular weight of approximately 22,500 daltons. It is produced by recombinant DNA technology using genetically engineered Chinese Hamster Ovary cells into which the human interferon beta gene has been introduced. The amino acid sequence of REBIF is identical to that of natural fibroblast derived human interferon beta. Natural interferon beta and interferon beta-1a (REBIF) are glycosylated with each containing a single N-linked complex carbohydrate moiety.

Using a reference standard calibrated against the World Health Organization natural interferon beta standard (Second International Standard for Interferon, Human Fibroblast GB 23 902 531), REBIF has a specific activity of approximately 270 million international units (MIU) of antiviral activity per mg of interferon beta-1a determined specifically by an in vitro cytopathic effect bioassay using WISH cells and Vesicular Stomatitis virus. REBIF 8.8 mcg, 22 mcg and 44 mcg contains approximately 2.4 million international units, 6 million international units or 12 million international units, respectively, of antiviral activity using this method.

REBIF (interferon beta-1a) is formulated as a sterile solution in a prefilled syringe or REBIF Rebidose autoinjector intended for subcutaneous (sc) injection. Each 0.5 mL (0.5 cc) of REBIF contains either 22 mcg or 44 mcg of interferon beta-1a, 2 mg or 4 mg albumin (human), 27.3 mg mannitol, 0.4 mg sodium acetate, and water for injection. Each 0.2 mL (0.2 cc) of REBIF contains 8.8 mcg of interferon beta-1a, 0.8 mg albumin (human), 10.9 mg mannitol, 0.16 mg sodium acetate, and water for injection.

12 CLINICAL PHARMACOLOGY

12.1 Mechanism of Action

The mechanism(s) by which REBIF (interferon beta-1a) exerts its therapeutic effects in patients with multiple sclerosis is unknown.

12.2 Pharmacodynamics

The relationships between serum interferon beta-1a levels and measurable pharmacodynamic activities to the mechanism(s) by which REBIF exerts its effects in multiple sclerosis are unknown. No gender-related effects on pharmacodynamic parameters have been observed.

12.3 Pharmacokinetics

The pharmacokinetics of REBIF (interferon beta-1a) in people with multiple sclerosis have not been evaluated. In healthy subjects, a single subcutaneous (sc) injection of 60 mcg of REBIF (liquid formulation) resulted in a peak serum concentration (Cmax) of 5.1 ± 1.7 IU/mL (mean ± SD), with a median time of peak serum concentration (Tmax) of 16 hours. The serum elimination half-life (t1/2) was 69 ± 37 hours, and the area under the serum concentration versus time curve (AUC) from zero to 96 hours was 294 ± 81 IU h/mL. Following every other day sc injections in healthy subjects, an increase in AUC of approximately 240% was observed, suggesting that accumulation of interferon beta-1a occurs after repeat administration. Total clearance is approximately 33-55 L/hour. There have been no observed gender-related effects on pharmacokinetic parameters. Pharmacokinetics of REBIF in pediatric and geriatric patients or patients with renal or hepatic insufficiency have not been established.

13 NONCLINICAL TOXICOLOGY

13.1 Carcinogenesis, Mutagenesis, Impairment of Fertility

Carcinogenesis: REBIF has not been tested for carcinogenic potential in animals.

Mutagenesis: Interferon beta was negative in an in vitro bacterial reverse mutation (Ames) assay and an in vitro cytogenetic assay in human lymphocytes in the presence and absence of metabolic activation.

Impairment of Fertility: In studies in normally cycling female cynomolgus monkeys given daily subcutaneous injections of interferon beta for six months at doses of up to 9 times the recommended weekly human dose (based on body surface area), no effects were observed on either menstrual cycling or serum estradiol levels. In male monkeys, the same doses of interferon beta had no demonstrable adverse effects on sperm count, motility, morphology, or function.

14 CLINICAL STUDIES

Two multicenter studies evaluated the safety and efficacy of REBIF in patients with relapsing-remitting multiple sclerosis.

Study 1 was a randomized, double-blind, placebo controlled study in patients with multiple sclerosis for at least one year, Kurtzke Expanded Disability Status Scale (EDSS) scores ranging from 0 to 5, and at least 2 acute exacerbations in the previous 2 years. Patients with chronic progressive forms of multiple sclerosis were excluded from the study. Patients received subcutaneous injections of either placebo (n = 187), REBIF 22 mcg (n = 189), or REBIF 44 mcg (n = 184) administered three times per week for two years. Doses of study agents were progressively increased to their target doses during the first 4 to 8 weeks for each patient in the study [see Dosage and Administration (2.1)].

The primary efficacy endpoint was the number of clinical exacerbations. Numerous secondary efficacy endpoints were also evaluated and included exacerbation-related parameters, effects of treatment on progression of disability and magnetic resonance imaging (MRI)-related parameters. Progression of disability was defined as an increase in the EDSS score of at least one point sustained for at least 3 months. Neurological examinations were completed every 3 months, during suspected exacerbations, and coincident with MRI scans. All patients underwent proton density T2-weighted (PD/T2) MRI scans at baseline and every 6 months. A subset of 198 patients underwent PD/T2 and T1-weighted gadolinium-enhanced (Gd)-MRI scans monthly for the first 9 months. Of the 560 patients enrolled, 533 (95%) provided 2 years of data and 502 (90%) received 2 years of study agent.

Study results are shown in Table 4 and Figure 1. REBIF at doses of 22 mcg and 44 mcg administered three times per week significantly reduced the number of exacerbations per patient as compared to placebo. Differences between the 22 mcg and 44 mcg groups were not significant (p >0.05).

Table 4: Clinical and MRI Endpoints from Study 1
 | Placebo | REBIF 22 mcg | REBIF 44 mcg
 | n = 187 | n = 189 | n = 184
Exacerbation-related
Mean number of exacerbations per patient over 2 years [Intent-to-treat analysis] , [Poisson regression model adjusted for center and time on study] | 2.56 | 1.82 [p<0.001 compared to placebo] | 1.73 [p<0.0001 compared to placebo]
(Percent reduction) |  | (29%) | (32%)
Percent (%) of patients exacerbation-free at 2 years [Logistic regression adjusted for center. Patients lost to follow-up prior to an exacerbation were excluded from this analysis. (Analysis included 185, 183, and 184 patients for three times per week placebo, 22 mcg REBIF, and 44 mcg REBIF, respectively).] | 15% | 25% [p<0.05 compared to placebo] | 32%
Median time to first exacerbation (months), [Cox proportional hazard model adjusted for center] | 4.5 | 7.6 | 9.6
MRI | n = 172 | n = 171 | n = 171
Median percent (%) change of MRI PD-T2 lesion area at 2 years [ANOVA on ranks adjusted for center. Patients with missing scans were excluded from this analysis.] | 11.0% | -1.2% | -3.8%
Median number of active lesions per patient per scan (PD/T2; 6 monthly) | 2.25 | 0.75 | 0.5

The time to onset of progression in disability sustained for three months was significantly longer in patients treated with REBIF than in placebo-treated patients. The Kaplan-Meier estimates of the proportions of patients with sustained disability are depicted in Figure 1.

Figure 1: Proportions of Patients with Sustained Disability Progression

Study 2 was a randomized, open-label, evaluator-blinded, active comparator study. Patients with relapsing-remitting multiple sclerosis with EDSS scores ranging from 0 to 5.5, and at least 2 exacerbations in the previous 2 years were eligible for inclusion. Patients with chronic progressive forms of multiple sclerosis were excluded from the study. Patients were randomized to treatment with three times per week subcutaneous injections of REBIF 44 mcg (n=339) or once weekly intramuscular injections of 30 mcg AVONEX (n=338). Study duration was 48 weeks.

The primary efficacy endpoint was the proportion of patients who remained exacerbation-free at 24 weeks. The principal secondary endpoint was the mean number per patient per scan of combined unique active MRI lesions through 24 weeks, defined as any lesion that was T1 active or T2 active. Neurological examinations were performed every three months by a neurologist blinded to treatment assignment. Patient visits were conducted monthly, and mid-month telephone contacts were made to inquire about potential exacerbations. If an exacerbation was suspected, the patient was evaluated with a neurological examination. MRI scans were performed monthly and analyzed in a treatment-blinded manner.

Patients treated with REBIF 44 mcg three times per week were more likely to remain relapse-free at 24 and 48 weeks than were patients treated with AVONEX 30 mcg once per week (Table 5). This study does not support any conclusion regarding effects on the accumulation of physical disability.

Table 5: Clinical and MRI Results from Study 2
 | REBIF 44 mcg | AVONEX 30 mcg | Absolute Difference | Risk of relapse on REBIF relative to AVONEX
Relapses | N=339 | N=338
Proportion of patients relapse-free at 24 weeks [Logistic regression model adjusted for treatment and center, intent to treat analysis] | 75% [p <0.001 (REBIF compared to AVONEX)] | 63% | 12% (95% CI: 5%, 19%) | 0.68 (95% CI: 0.54, 0.86)
Proportion of patients relapse-free at 48 weeks | 62% [p = 0.009 (REBIF compared to AVONEX)] | 52% | 10% (95% CI: 2%, 17%) | 0.81 (95% CI: 0.68, 0.96)
MRI (through 24 weeks) | N=325 | N=325
Median of the mean number of combined unique MRI lesions per patient per scan [Nonparametric ANCOVA model adjusted for treatment and center, with baseline combined unique lesions as the single covariate] (25th, 75th percentiles) | 0.17 (0.00, 0.67) | 0.33 (0.00, 1.25)

16 HOW SUPPLIED/STORAGE AND HANDLING

REBIF is supplied as a sterile solution containing no preservative available in the following package presentations:

Prefilled Syringes:

REBIF (interferon beta -1a) Titration Pack, NDC 44087-8822-1
  - Six REBIF 8.8 mcg prefilled syringes and Six REBIF 22 mcg prefilled syringes
REBIF (interferon beta -1a) 22 mcg Prefilled syringe
  - Twelve REBIF 22 mcg prefilled syringes, NDC 44087-0022-3
REBIF (interferon beta -1a) 44 mcg Prefilled syringe
  - Twelve REBIF 44 mcg prefilled syringes, NDC 44087-0044-3

REBIF Rebidose Autoinjectors:

REBIF Rebidose (interferon beta-1a) Titration Pack, NDC 44087-0188-1
  - Six REBIF Rebidose 8.8 mcg autoinjectors with lime-green injector buttons and Six REBIF Rebidose 22 mcg with yellow injector buttons.
REBIF Rebidose (interferon beta-1a) 22 mcg Autoinjector
  - Twelve REBIF Rebidose 22 mcg autoinjectors with yellow injector buttons, NDC 44087-3322-1
REBIF Rebidose (interferon beta-1a) 44 mcg Autoinjector
  - Twelve REBIF Rebidose 44 mcg autoinjectors with teal-green injector buttons, NDC 44087-3344-1

STORAGE AND HANDLING

REBIF should be stored refrigerated between 36°F to 46°F (2°C to 8°C). DO NOT FREEZE. If needed, REBIF may be stored between 36°F to 77°F (2°C to 25°C) for up to 30 days and away from heat and light, but refrigeration is preferred.

Do not use beyond the expiration date printed on packages. REBIF contains no preservatives. Each prefilled syringe and REBIF Rebidose autoinjector is intended for a single dose. Unused portions should be discarded.

17 PATIENT COUNSELING INFORMATION

See FDA-approved patient labeling (Medication Guide).

Inform patients of the availability of a Medication Guide, and instruct them to read the Medication Guide prior to taking REBIF. Instruct patients to take REBIF only as prescribed.

Depression and Suicide

Advise patients that depression, suicidal ideation, and suicide have been reported during the use of REBIF. Inform patients of the symptoms of depression and suicidal ideation and instruct patients to immediately report any of these symptoms to their healthcare provider [see Warnings and Precautions (5.1)].

Hepatic Injury

Advise patients that severe liver injury, including hepatic failure, has been reported with the use of REBIF. Educate patients about the symptoms of hepatic injury and instruct patients to report them immediately to their healthcare provider [see Warnings and Precautions (5.2)].

Anaphylaxis and Other Allergic Reactions

Advise patients of the symptoms of allergic reactions and anaphylaxis, and instruct patients to seek immediate medical attention if these symptoms occur [see Warnings and Precautions (5.3)].

Injection Site Reactions Including Necrosis

Advise patients that injection site reactions occur in most patients treated with REBIF and that injection site necrosis may occur [see Warnings and Precautions (5.4)]. Instruct patients to promptly report any break in the skin, which may be associated with blue-black discoloration, swelling, or drainage of fluid from the injection site, prior to continuing their REBIF therapy.

To minimize the likelihood of injection site reactions, inform patients of the importance of rotating injection sites with each dose and the use of aseptic injection technique [see Dosage and Administration (2.2)]. Advise patients not to re-use needles or syringes and instruct patients on safe disposal procedures. Provide appropriate instruction for self-injection of REBIF and REBIF Rebidose, including careful review of the REBIF Medication Guide.

Decreased Peripheral Blood Counts

Advise patients that they may develop a lowering of their peripheral blood counts, including their white blood counts, red blood counts, and platelets, and that their blood counts will be checked during therapy with REBIF. Inform patients that they may be more likely to get infections, anemia, or be at risk for bleeding, and that they should contact their healthcare provider if they develop symptoms of these adverse reactions [see Warnings and Precautions (5.5)].

Pulmonary Arterial Hypertension

Inform patients that PAH has occurred in patients treated with interferon beta products, including REBIF. Instruct patients to promptly report any new symptoms such as new or increasing fatigue or shortness of breath to their healthcare provider [see Warnings and Precautions (5.7)].

Seizures

Instruct patients to report seizures immediately to their healthcare provider [see Warnings and Precautions (5.8)].

Flu-like Symptoms

Inform patients that flu-like symptoms are common following initiation of therapy with REBIF. Advise patients that concurrent use of analgesics and/or antipyretics may help reduce flu-like symptoms on treatment days [see Dosage and Administration (2.3)].

Pregnancy

Advise patients to notify their healthcare provider if they become pregnant during treatment or plan to become pregnant [see Use in Specific Populations (8.1)].

Manufactured by EMD Serono, Inc. Boston, MA 02210
U.S. License # 1773

Marketed by:

EMD Serono, Inc.
Boston, MA 02210

*AVONEX is a registered trademark of Biogen

MEDICATION GUIDE REBIF (interferon beta-1a) Injection for subcutaneous use

Read this Medication Guide before you start using REBIF and each time you get a refill. There may be new information. The information does not take the place of talking with your healthcare provider about your medical condition or your treatment.

What is the most important information I should know about REBIF?

REBIF can cause serious side effects. Tell your healthcare provider right away if you have any of the symptoms listed below while taking REBIF.

1. Behavioral health problems including depression and suicidal thoughts. You may have mood problems including:
  - depression (feeling hopeless or feeling bad about yourself)
  - thoughts of hurting yourself or suicide
2. Liver problems or worsening of liver problems including liver failure. Symptoms may include:
  - nausea
  - loss of appetite
  - tiredness
  - dark colored urine and pale stools
  - yellowing of your skin or the white part of your eye
  - bleeding more easily than normal
  - confusion
  - sleepiness
  During your treatment with REBIF you will need to see your healthcare provider regularly and have regular blood tests to check for side effects.

3. Serious allergic and skin reactions. Symptoms may include:
  - itching
  - swelling of your face, eyes, lips, tongue or throat
  - trouble breathing
  - anxiousness
  - feeling faint
  - skin rash, hives, sores in your mouth, or skin blisters and peels

4. Injection site problems. REBIF may cause redness, pain, itching or swelling at the place where your injection was given. Call your healthcare provider right away if an injection site becomes swollen and painful or the area looks infected. You may have a skin infection or an area of severe skin damage (necrosis) requiring treatment by a healthcare provider.

What is REBIF?

REBIF is a prescription medicine used to treat relapsing forms of multiple sclerosis, to include clinically isolated syndrome, relapsing-remitting disease, and active secondary progressive disease, in adults. It is a form of protein called beta interferon that is produced in the body.

It is not known if REBIF is safe and effective in children.

Who should not take REBIF?

Do not take REBIF if you:

- are allergic to interferon beta, human albumin, or any of the ingredients in REBIF. See the end of this Medication Guide for a complete list of ingredients in REBIF.

What should I tell my healthcare provider before taking REBIF?

Before you take REBIF, tell your healthcare provider if you have or have had any of the following conditions:

- mental illness, including depression and suicidal behavior
- liver problems
- bleeding problems or blood clots
- low blood cell counts
- seizures (epilepsy)
- thyroid problems
- drink alcohol
- you are pregnant or plan to become pregnant. It is not known if REBIF can harm your unborn baby.
- you are breastfeeding or plan to breastfeed. REBIF may pass into your breastmilk. Talk with your healthcare provider about the best way to feed your baby if you take REBIF.

Tell your healthcare provider about all medicines you take, including prescription and over-the-counter medicines, vitamins and herbal supplements.

REBIF and other medicines may affect each other causing side effects.

Ask your healthcare provider or pharmacist for a list of these medicines, if you are not sure.

Know the medicines you take. Keep a list of them to show your healthcare provider and pharmacist when you get a new medicine.

How should I use REBIF?

- See the Instructions for Use at the end of this Medication Guide on how to prepare and give an injection of REBIF using a prefilled syringe. For the REBIF Rebidose autoinjector, read the Instructions for Use that comes with the REBIF Rebidose autoinjector.
- Your healthcare provider should show you how to prepare and measure your dose of REBIF and how to inject your REBIF before you use it for the first time.
- REBIF is given by injection under the skin (subcutaneous injection) on the same 3 days a week, for example, Monday, Wednesday and Friday.
- Your injections should be at least 48 hours apart. Take them the same time each day.
- Inject REBIF exactly as your healthcare provider tells you.
- Your healthcare provider will tell you how much REBIF to inject, and may change the dose based on how your body responds. Do not inject more than your healthcare provider tells you to.
- Do not change your dose unless your healthcare provider tells you to.
- Change (rotate) your injection site you choose with each injection. This will help decrease the chance that you will have an injection site reaction.
- Do not inject REBIF into an area of the body where the skin is irritated, reddened, bruised, infected or scarred in any way.
- REBIF comes as a:
  - prefilled syringe (REBIF)
  - single-use prefilled autoinjector (REBIF Rebidose autoinjector)
  Your healthcare provider will decide which is best for you. Always use a new, unopened, prefilled syringe of REBIF or REBIF Rebidose autoinjector for each injection. Do not reuse prefilled syringes or REBIF Rebidose autoinjectors.

What are the possible side effects of REBIF?

REBIF may cause serious side effects, including:

- See "What is the most important information I should know about REBIF?"
- Blood problems. REBIF can affect your bone marrow and cause low red and white blood cell, and platelet counts. In some people, these blood cell counts may fall to dangerously low levels. If your blood cell counts become very low, you can get infections and problems with bleeding and bruising. Your healthcare provider may ask you to have regular blood tests to check for blood problems.
- Pulmonary arterial hypertension. Pulmonary arterial hypertension can occur with interferon beta products, including REBIF. Symptoms may include new fatigue or shortness of breath. Contact your healthcare provider right away if you develop these symptoms.
- Seizures. Some people have had seizures while taking REBIF.

The most common side effects of REBIF include:

- flu-like symptoms. You may have flu-like symptoms when you first start taking REBIF. You may be able to manage these flu-like symptoms by taking over-the-counter pain and fever reducers. For many people, these symptoms lessen or go away over time. Symptoms may include:
  - muscle aches
  - fever
  - tiredness
  - chills
- stomach pain
- change in liver blood tests

Tell your healthcare provider if you have any side effect that bothers you or that does not go away.

These are not all the possible side effects of REBIF. For more information, ask your healthcare provider or pharmacist.

Call your doctor for medical advice about side effects. You may report side effects to the FDA at 1-800-FDA-1088.

How should I store REBIF?

- Store REBIF in the refrigerator between 36°F to 46°F (2°C to 8°C).
- Do not freeze REBIF.
- If you cannot refrigerate your REBIF, you can store your REBIF at temperatures above 36°F and below 77°F (2°C to 25°C) for up to 30 days.
- Keep REBIF away from heat and light.

Keep REBIF and all medicines out of the reach of children.

General information about the safe and effective use of REBIF

Medicines are sometimes prescribed for purposes other than those listed in a Medication Guide. Do not use REBIF for a condition for which it was not prescribed. Do not give REBIF to other people, even if they have the same symptoms that you have. It may harm them.

This Medication Guide summarizes the most important information about REBIF. If you would like more information, talk with your healthcare provider. You may ask your healthcare provider or pharmacist for information about REBIF that is written for healthcare professionals.

For more information, go to www.REBIF.com or call toll-free 1-877-447- 3243.

What are the ingredients in REBIF?

Active ingredient: interferon beta-1a

Inactive ingredients: albumin (human), mannitol, sodium acetate, water for injection

This Medication Guide has been approved by the U.S. Food and Drug Administration.

Revised 7/2023

Instructions for Use REBIF (Re-bif) (interferon beta-1a) (in-ter-feer-on beta-one-â) Injection for subcutaneous use Prefilled Syringe

Read and follow the Instructions for Use that come with your REBIF prefilled syringe before you start using it and each time you get a refill. Before you use a REBIF prefilled syringe for the first time, make sure your healthcare provider shows you the right way to use it.

Important: For the REBIF Rebidose autoinjector, read the Instructions for Use that come with the REBIF Rebidose autoinjector.

Parts of your REBIF Prefilled Syringe (See Figure A).

Figure A

Supplies needed for a REBIF Injection (See Figure B):

- REBIF prefilled syringe
- alcohol pad or cotton balls and rubbing alcohol
- small adhesive bandage strip if desired
- puncture resistant safety container for disposal of used syringes. See "Disposing of your Needles and Syringes Section" in Step 4 of the IFU.
- antibacterial soap
- an over-the-counter pain or fever reducing medicine, if your healthcare provider has recommended that you take this before, at the same time, or after you give yourself REBIF to help decrease the fever, chills, sweating and muscle aches (flu-like symptoms) that may happen.

Figure B

Titration (Dosing) Schedule

- When first starting treatment with REBIF, your healthcare provider may prescribe either the 22 mcg or 44 mcg dose of REBIF. You should gradually increase the dose over 4 weeks, starting at 20% of the prescribed dose for the first 2 weeks, half-dose for the second 2 weeks (weeks 3 and 4), and then the full dose prescribed by your healthcare provider.

If your prescribed dose is 22 mcg of REBIF, a REBIF Titration Pack containing 6 prefilled syringes with 8.8 mcg and 6 prefilled syringes with 22 mcg should be prescribed to you for use during the 4-week starting period. Table 1 explains the amount to inject using the REBIF Titration Pack syringes to gradually increase to 22 mcg.

Table 1: Titration Schedule for a 22 mcg Prescribed Dose [Only prefilled syringes can be used to titrate to the 22 mcg Prescribed Dose]
Week of Use | Syringe to Use | Amount of syringe
Week 1 Titration | 8.8 mcg syringe | Use half of syringe
Week 2 Titration | 8.8 mcg syringe | Use half of syringe
Week 3 Titration | 22 mcg syringe | Use half of syringe
Week 4 Titration | 22 mcg syringe | Use half of syringe
Week 5 and on | 22 mcg syringe or autoinjector | Use full syringe or autoinjector

If your prescribed dose is 44 mcg, you may be prescribed either a REBIF Titration Pack (described above) or REBIF Rebidose Titration Pack containing 6 autoinjectors with 8.8 mcg and 6 autoinjectors with 22 mcg for use during the 4 week titration period. Table 2 explains the amount to inject using the REBIF Titration Pack or REBIF Rebidose Titration Pack to gradually increase to 44 mcg.

Table 2: Titration Schedule for a 44 mcg Prescribed Dose [Prefilled syringes or autoinjectors can be used to titrate to 44 mcg Prescribed Dose]
Week of Use | Syringe or Autoinjector to Use | Amount of syringe or autoinjector
Week 1 Titration | 8.8 mcg syringe or autoinjector | Use full syringe or autoinjector
Week 2 Titration | 8.8 mcg syringe or autoinjector | Use full syringe or autoinjector
Week 3 Titration | 22 mcg syringe or autoinjector | Use full syringe or autoinjector
Week 4 Titration | 22 mcg syringe or autoinjector | Use full syringe or autoinjector
Week 5 and on | 44 mcg syringe or autoinjector | Use full syringe or autoinjector

Step 1. Preparing for your REBIF Injection

- Check the expiration date. Do not use if the medication is expired. The expiration date is printed on the syringe, plastic syringe packaging and carton.
- Remove your REBIF syringe from the refrigerator at least 30 minutes before you plan to use it so it can warm to room temperature. Do not heat or microwave the medication.
- Be sure that the dose, either, 8.8 mcg, 22 mcg or 44 mcg, described on the carton is the same as the dose prescribed by your healthcare provider.
- Remove the REBIF syringe from the plastic packaging. Keep the needle capped.
- Look at the contents of the syringe carefully. The liquid should be clear to slightly yellow. Do not use if the liquid is cloudy, discolored or contains particles. Use a different syringe.

Step 2. Choose and Prepare your Injection Site

- The best sites for giving yourself an injection are those areas with a layer of fat between the skin and muscle, like your thigh, the outer surface of your upper arm, your stomach or buttocks.
- Do not use the area near your waistline or within 2 inches of your navel. If you are very thin, use only the thigh or outer surface of the arm for injection.
- Use a different site each time you inject such as the thigh, hip, stomach or upper arm (See Figure C).
  Figure C
- Do not inject REBIF into an area of your body where the skin is irritated, reddened, bruised, infected or abnormal in any way.
- Wash your hands thoroughly with antibacterial soap before preparing to inject the medicine.
- Clean the injection site with an alcohol pad or cotton ball with rubbing alcohol using a circular motion. To avoid stinging, you should let your skin dry before you inject REBIF.

Step 3. Inject your REBIF

- Remove the needle cap from the syringe needle.
- If your healthcare provider has told you to use less than the full 0.5 mL dose, slowly push the plunger in until the amount of medicine left in the syringe is the amount healthcare provider told you to use.
- Use your thumb and forefinger to pinch a pad of skin surrounding the cleaned injection site (See Figure D). Hold the syringe like a pencil with your other hand.
  Figure D
- While still pinching the skin, quickly insert the needle like a dart at about a 90 degree angle (just under the skin) into the pad of tissue as shown (See Figure E).
  Figure E
- After the needle is in, remove the hand that you used to pinch your skin and inject the medicine using a slow, steady push on the plunger until all the medicine is injected and the syringe is empty (See Figure F).
  Figure F
- Withdraw the needle and apply gentle pressure to the injection site with a dry cotton ball or sterile gauze. Applying a cold compress or ice pack to the injection site after injection may help reduce local skin reactions.
- Put a small adhesive bandage strip over the injection site, if desired.
- Keep a record of the date and location of each injection.
- After 2 hours, check the injection site for redness, swelling, or tenderness. If you have a skin reaction and it does not clear up in a few days, call your healthcare provider.

Step 4. Disposing of your Needles and Syringes

- Put your used needles, syringes, and autoinjectors, including REBIF, in an FDA-cleared sharps container right away after use. Do not throw away (dispose of) any syringes or autoinjectors in your household trash.
  If you do not have an FDA-cleared sharps disposal container, you may use a household container that is:
  - made of a heavy-duty plastic,
  - closed with a tight-fitting, puncture-resistant lid,
  - upright and stable during use,
  - leak-resistant, and
  - properly labeled to warn of hazardous waste inside the container.
- When your sharps disposal container is almost full, you will need to follow your community guidelines for the right way to dispose of your sharps disposal container. There may be state or local laws about how you should throw away used autoinjectors and syringe needles. For more information about safe sharps disposal, and for specific information about sharps disposal in the state that you live in, go to the FDA's website at: http://www.fda.gov/safesharpsdisposal.
- Do not dispose of your used sharps disposal container in your household trash unless your community guidelines permit this. Do not recycle your used sharps disposal container.

Manufactured by:
EMD Serono, Inc.
Boston, MA 02210
U.S. License 1773

Marketed by:
EMD Serono, Inc.
Boston, MA 02210

Revised 02/2025

INSTRUCTIONS FOR USE

Rebif® Rebidose®

Instructions For Use

Exclusively for use with
Rebif®
(interferon beta-1a)
subcutaneous injection

Welcome

This guide contains information on how to use Rebif® Rebidose®, a pre-assembled, single-use autoinjector that administers one dose of Rebif® (interferon beta-1a) for the treatment of relapsing forms of multiple sclerosis.

Please read these instructions carefully before you start using the Rebif® Rebidose® and remember, you must have received the appropriate training before injecting.

If at any time, you have questions or concerns, please contact your health care provider or call MS LifeLines at 1-877-447-3243.

Rx Only

Contents
Rebif® Rebidose® features | 4
Warnings | 6
Important Information | 8
How Supplied | 10
Titration | 12
Choosing an injection site | 13
Step 1: Prepare for your injection | 14
Examine syringe and expiration date | 15
Step 2: Administer your injection | 18
Step 3: Finish your injection | 20
Disposal | 22
Storage | 25
Travel | 26
Notes | 27

Rebif® Rebidose® features

Before injection:

After injection:

Warnings

- Always use the injection technique advised by your health care provider and contact them with any questions you might have.
- Always keep the Rebidose® autoinjector out of the reach of children.
- Do not share the Rebidose® with anyone. Doing so may result in injury, including the transmission of infectious blood-borne diseases. Adhere to strict safety and antiseptic precautions at all times.
  - Do not insert your fingers into the opening of the safety guard.
  - Do not try to re-use a Rebidose® single-use autoinjector that has already been used.
  - Adhere to proper disposal procedures to avoid a needle stick injury.
- Check the expiration date on the Rebidose® autoinjector label and its carton. If the medication has expired, Do not use it.
- Examine the contents of the syringe carefully through the transparent housing. The liquid should be clear or slightly yellow. Inspect for cracks or breakage in the syringe or other parts. Do not use Rebidose® if it is cracked or broken or if the liquid is cloudy, discolored or contains particles.
- If the Rebidose® has been dropped more than 3 feet, or if it looks damaged for any reason, Do not use it. Instead, dispose of it in an acceptable biohazard (sharps) container and use a new Rebidose® autoinjector.
- Contact your health care provider about any damaged Rebidose® autoinjector.

Important Information

- Store your Rebidose® autoinjectors in a refrigerator until ready for use.
- If you or someone around you is injured by the needle, contact your health care provider immediately and dispose of the Rebidose® in an acceptable biohazard (sharps) container.
- Injecting Rebif® the medicine in the Rebidose® autoinjector may cause skin reactions including soreness, redness, pain, bruising, or swelling. Tell your health care provider about any skin reactions that become swollen, painful, or look infected and do not heal within a few days.
- Use a different site each time you inject. Do not inject Rebif® where your skin is irritated, reddened, bruised, infected or abnormal in any way.
- The Rebidose® autoinjector contains a glass syringe. In very rare cases, the syringe may break during the injection. If this happens, immediately dispose of any broken glass and the damaged Rebidose® autoinjector in the biohazard (sharps) container, taking necessary precautions to avoid injury. Contact your health care provider or MS LifeLines at 1-877-447-3243 immediately.

How Supplied

Rebidose® is available in 3 dose sizes. Check that the dose of Rebif® is the one prescribed for you by looking at the Rebidose® carton and at the dose label on the Rebidose® autoinjector.

Rebidose® autoinjectors are supplied in these 3 packaging presentations:

- Titration Pack
  - 6 Rebif® 8.8 mcg Rebidose® autoinjectors with a lime green injector button.
  - 6 Rebif® 22 mcg Rebidose® autoinjectors with a yellow injector button.
- 12 Rebif® 22 mcg Rebidose® autoinjectors with a yellow injector button.
- 12 Rebif® 44 mcg Rebidose® autoinjectors with a teal green injector button.

Titration

At the beginning of Rebif® treatment, your health care provider may prescribe a titration phase to gradually increase to the intended dosage.

The Rebif® Titration Pack contains six 8.8 mcg Rebidose® autoinjectors with a lime green injector button and six 22 mcg Rebidose® autoinjectors with a yellow injector button.

The titration period lasts 4 weeks and during this time, you will administer 12 injections:

- Weeks 1 and 2: Use one 8.8 mcg autoinjector three times a week, at least 48 hours apart.
- Weeks 3 and 4: Use one 22 mcg autoinjector three times a week, at least 48 hours apart.

Your health care provider may provide a different dose and schedule.

Choosing an injection site

The best sites for giving a subcutaneous injection are those areas with a layer of fat between the skin and muscle. These include the thigh, the outer surface of the upper arm, the stomach and the buttocks. Do not use the area near your waistline or within 2 inches of your navel.

Only choose one site for injection. Use a different site each time you inject.

- - - - - - - - - - - - - - - - - - - - - - - - - - - - - - - - - - - - - - - - - - - - - - - - - - - - - - - - - - - - - - - - - - - - - - -

Caution

Do not inject Rebif® where your skin is irritated, reddened, bruised, infected or abnormal in any way.

- - - - - - - - - - - - - - - - - - - - - - - - - - - - - - - - - - - - - - - - - - - - - - - - - - - - - - - - - - - - - - - - - - - - - - -

Step 1: Prepare for your injection

1.1) Before you begin, you may find injecting more comfortable if you allow time for the Rebif® to warm up to room temperature before injecting. Therefore, it is recommended that you remove the Rebidose® autoinjector from the refrigerator at least 30 minutes prior to use.

- - - - - - - - - - - - - - - - - - - - - - - - - - - - - - - - - - - - - - - - - - - - - - - - - - - - - - - - - - - - - - - - - - - - - - -

Caution

Do not heat or microwave a Rebidose® autoinjector.

- - - - - - - - - - - - - - - - - - - - - - - - - - - - - - - - - - - - - - - - - - - - - - - - - - - - - - - - - - - - - - - - - - - - - - -

1.2) Put all of the items listed below within easy reach on a table or other stable surface:

- 1 Rebidose® autoinjector containing Rebif®
- Alcohol wipes/swabs or cotton balls and rubbing alcohol
- Small adhesive bandage strip (if needed)
- A biohazard (sharps) container (see Disposal section on page 22)

1.3) Wash your hands thoroughly with antibacterial soap.

1.4) Open the tray over a table or soft surface by peeling back the plastic covering and remove 1 Rebidose® autoinjector. Do not remove the needle cap until you are ready to inject because the autoinjector could roll off the table and become unsterile.

1.5) Check the expiration date on the Rebidose® autoinjector label and its carton. If the medication has expired, do not use it.

1.6) Examine the contents of the syringe carefully through the transparent housing. The liquid should be clear or slightly yellow.

1.7) Inspect for cracks or breakage in the syringe or other parts. Do not use Rebidose® if it is cracked or broken or if the liquid is cloudy, discolored or contains particles.

1.8) Use an alcohol wipe to clean the injection site. Let your skin dry to prevent stinging during injection.

1.9) Hold the Rebidose® by the injector body (fig a) and pull off the needle cap.

1.10) Look inside the needle cap to make sure you see a black needle shield inside the cap (fig b).

1.11) Dispose of the needle cap and proceed to the injection step without delay.

Warning
If the Rebidose® has been dropped more than 3 feet, or if it looks damaged for any reason, do not use it. Instead, dispose of it in an acceptable biohazard (sharps) container and use a new Rebidose® autoinjector.

Step 2: Administer your injection

2.1) Hold the Rebidose® autoinjector in your palm with your thumb above the injector button.

2.2) Place the Rebidose® upright with the needle end flat against your skin at a 90° angle. Push the Rebidose® against your skin until you feel resistance; this action unlocks the injector button (fig c).

2.3) Keep the Rebidose® pressed firmly against the skin and use your thumb to push the injector button (fig d). You will hear a click, which means the injection has begun.

2.4) Keep the Rebidose® pressed firmly against your skin for at least 10 seconds while the medication is dispensed (fig e).

If you have any problems, contact MS LifeLines at 1-877-447-3243.

Caution

If the injection does not start, release the injector button and make sure that the Rebidose® is still pressed firmly against your skin. Then push firmly on the injector button, listening for the click that indicates the start of the injection.

- - - - - - - - - - - - - - - - - - - - - - - - - - - - - - - - - - - - - - - - - - - - - - - - - - - - - - - - - - - - - - - - - - - - - - -

Step 3: Finish your injection

3.1) Before lifting the Rebidose® from your skin, make sure that the syringe plunger has moved to the bottom and that the entire dose has been injected (fig f).

3.2) Lift the Rebidose® from the injection site. The safety guard slides down and locks into place to protect you from the needle (fig g). If any liquid is left in the syringe or if you have any other problems, contact your health care provider or MS LifeLines at 1-877-447-3243.

Do not try to put the needle cap on the used Rebidose® autoinjector. It is no longer needed.

3.3) If desired, use a small adhesive bandage to cover the injection site.

Disposal

1) Put your used Rebidose® autoinjectors in a FDA-cleared sharps disposal container right away after use (fig h). Do not throw them away (dispose of) in your household trash.

2) If you do not have a FDA-cleared sharps disposal container, you may use a household container that is:

- made of a heavy-duty plastic;
- can be closed with a tight-fitting, puncture-resistant lid, without sharps being able to come out;
- upright and stable during use;
- leak-resistant; and
- properly labeled to warn of hazardous waste inside the container.

3) When your sharps disposal container is almost full, you will need to follow your community guidelines for the correct way to dispose of it. There may be state or local laws about how you should throw away used needles and syringes. For more information about safe sharps disposal in the state that you live in, go to the FDA's website at: http://www.fda.gov/safesharpsdisposal

4) Do not dispose of your used sharps disposal container in your household trash unless your community guidelines permit this. Do not recycle your used sharps disposal container.

- - - - - - - - - - - - - - - - - - - - - - - - - - - - - - - - - - - - - - - - - - - - - - - - - - - - - - - - - - - - - - - - - - - - - - -

Caution

Always keep the biohazard (sharps) container out of the sight and reach of children.

- - - - - - - - - - - - - - - - - - - - - - - - - - - - - - - - - - - - - - - - - - - - - - - - - - - - - - - - - - - - - - - - - - - - - - -

Warning

- Do not insert your fingers into the opening of the safety guard.
- Do not try to re-use a Rebidose® single-use autoinjector that has already been used.
- Adhere to proper disposal procedures to avoid a needle stick injury.

Storage

- Each Rebidose® autoinjector contains a single dose of Rebif®.
- Store Rebidose® autoinjectors in the refrigerator between 36°F and 46°F (2°C to 8°C). Do not freeze. If a refrigerator is not available, Rebidose® may be stored between 36˚F and 77˚F (2˚C to 25˚C) for up to 30 days away from heat and light.
- Do not put them in or near the freezer compartment. Do not inject Rebif® that you know or suspect has been frozen.
- Keep the Rebidose® in its packaging and only open one when you need it. Refer to the Rebif® drug package insert and medication guide for specific storage guidelines.

Travel

- When you travel, take 3 Rebidose® autoinjectors with you for each week of your trip. Take some extra in case you are away for longer than expected.
- Remember to pack an empty biohazard (sharps) container for proper disposal.
- When traveling by air, always carry Rebidose® autoinjectors in your hand luggage because the aircraft luggage compartment can be very cold and the Rebif® could freeze.
- It is safe to pass Rebidose® autoinjectors through x-ray machines, but you may need a note from your health care provider to allow you to carry them aboard an airplane.
- Prior to traveling, always check with your airline and your health care provider about bringing injectable medication with you.

Notes

You may find it helpful to record information about your 3 weekly injections (Inj.) to discuss with your health care provider.

Week 1 | Inj. Site | Date& Time | Site Reaction
Inj. 1 |  |  | Yes | No
Inj. 2 |  |  | Yes | No
Inj. 3 |  |  | Yes | No
Week 2 | Inj. Site | Date& Time | Site Reaction
Inj. 1 |  |  | Yes | No
Inj. 2 |  |  | Yes | No
Inj. 3 |  |  | Yes | No
Week 3 | Inj. Site | Date& Time | Site Reaction
Inj. 1 |  |  | Yes | No
Inj. 2 |  |  | Yes | No
Inj. 3 |  |  | Yes | No
Week 4 | Inj. Site | Date& Time | Site Reaction
Inj. 1 |  |  | Yes | No
Inj. 2 |  |  | Yes | No
Inj. 3 |  |  | Yes | No

This Instructions for Use has been approved by the Food and Drug Administration.

Version: December 2015
Manufacturer: EMD Serono, Inc.
Rockland, MA 02730 U.S. Lic. 1773
MS LifeLines: 1-877-447-3243

EMD Serono

N67Z0105C

EMD Serono, Inc. is an
affiliate of Merck KGaA,
Darmstadt, Germany

EMD

PRINCIPAL DISPLAY PANEL - Kit Carton - 8822

Rebif® Titration Pack
(interferon beta-1a)

NDC 44087-8822-1

8.8 mcg/0.2 mL
22 mcg/0.5 mL

For subcutaneous injection
Rx Only
Medication Guide for patients enclosed

6 single-dose 8.8 mcg/0.2 mL prefilled syringes
6 single-dose 22 mcg/0.5 mL prefilled syringes

EMD
Serono

PRINCIPAL DISPLAY PANEL - Kit Carton - 0188

Rebif® Rebidose®
(interferon beta-1a)
Injection

NDC 44087-0188-1

6 single-use 8.8 mcg / 0.2 mL autoinjectors
6 single-use 22 mcg / 0.5 mL autoinjectors

Rx only

8.8 mcg / 0.2 mL
22 mcg / 0.5 mL

Titration Pack
For subcutaneous injection

Attention pharmacist:
Each patient is required to receive
the enclosed Medication Guide

EMD
Serono

PRINCIPAL DISPLAY PANEL - 12 Syringe Carton - 0022

Rebif® 22 mcg/0.5 mL
(interferon beta-1a)

NDC 44087-0022-3

For subcutaneous injection
Rx only
Medication Guide for patients enclosed

12 single-dose prefilled syringes

EMD
SERONO

PRINCIPAL DISPLAY PANEL - 12 Syringe Carton - 0044

Rebif® 44 mcg/0.5 mL
(interferon beta-1a)

NDC 44087-0044-3

For subcutaneous injection
Rx only
Medication Guide for patients enclosed

12 single-dose prefilled syringes

EMD
SERONO

PRINCIPAL DISPLAY PANEL - 12 Autoinjector Carton - 3322

NDC 44087-3322-1

Rebif® Rebidose®
(interferon beta-1a)
Injection

12 single-use autoinjectors

22 mcg / 0.5 mL

Rx only

For subcutaneous injection

Attention pharmacist: Each patient is required
to receive the enclosed Medication Guide

EMD
Serono

PRINCIPAL DISPLAY PANEL - 12 Autoinjector Carton - 3344

NDC 44087-3344-1

Rebif® Rebidose®
(interferon beta-1a)
Injection

12 single-use autoinjectors

44 mcg / 0.5 mL

Rx only

For subcutaneous injection

Attention pharmacist: Each patient is required
to receive the enclosed Medication Guide

EMD
Serono